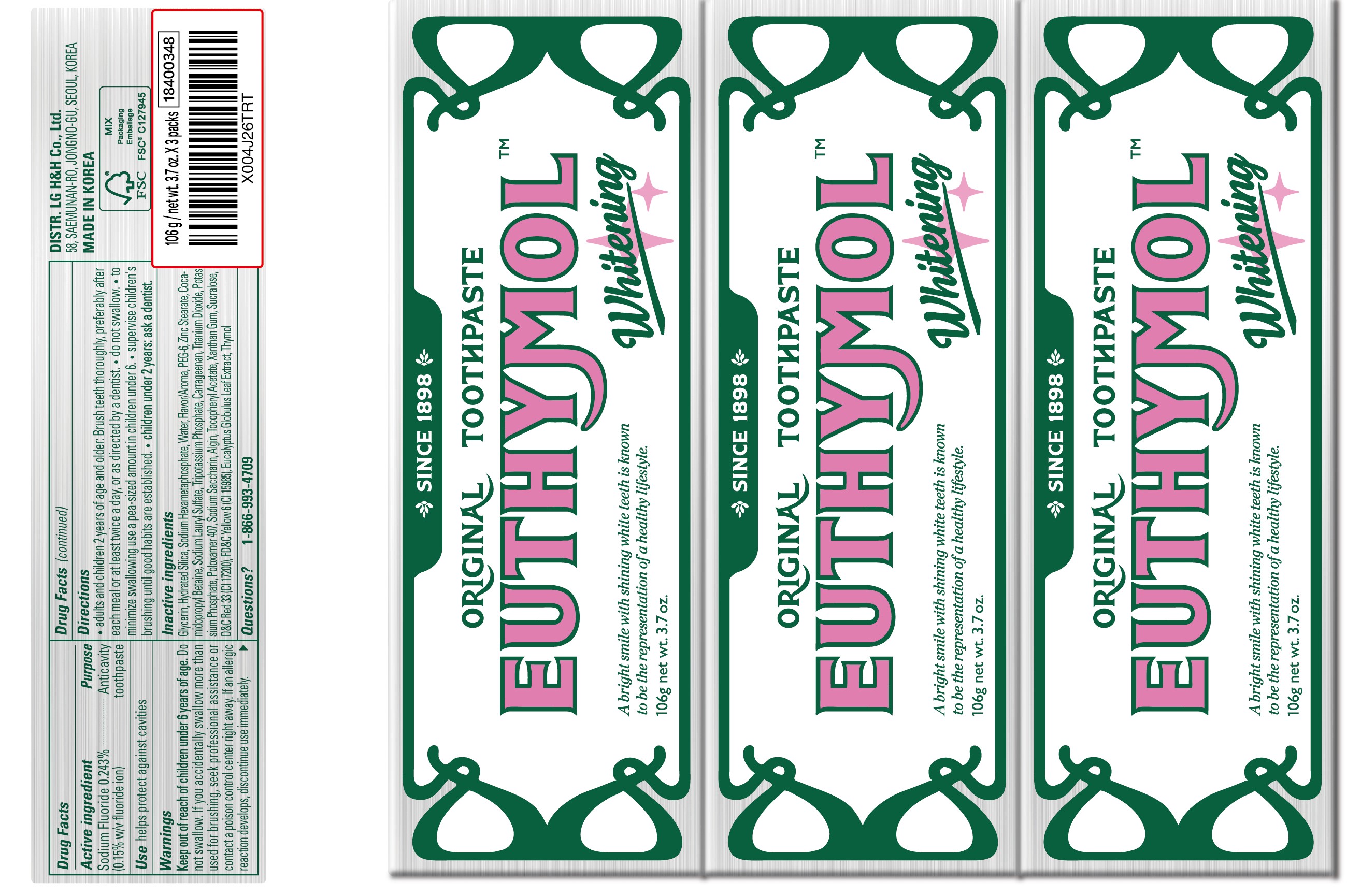 DRUG LABEL: Euthymol Whitening
NDC: 53208-566 | Form: PASTE, DENTIFRICE
Manufacturer: LG HOUSEHOLD & HEALTH CARE LTD.
Category: otc | Type: HUMAN OTC DRUG LABEL
Date: 20250903

ACTIVE INGREDIENTS: SODIUM FLUORIDE 1.5 mg/1 g
INACTIVE INGREDIENTS: POTASSIUM PHOSPHATE, TRIBASIC; ALGIN; XANTHAN GUM; HYDRATED SILICA; SODIUM SACCHARIN; ZINC STEARATE; SODIUM LAURYL SULFATE; TITANIUM DIOXIDE; THYMOL; COCAMIDOPROPYL BETAINE; POLOXAMER 407; .ALPHA.-TOCOPHEROL ACETATE; GLYCERIN; SUCRALOSE; RED 33; YELLOW 6; EUCALYPTUS GLOBULUS LEAF; SODIUM HEXAMETAPHOSPHATE; WATER; PEG-6; CARRAGEENAN; POTASSIUM PHOSPHATE

Active Ingredients

Sodium Fluoride 0.243%

(0.15% w/v fluoride ion)

Purpose

Anticavity toothpaste

Use

helps protect against cavities

WARNINGS

Keep out of reach of children under 6 years of age.

DOSAGE AND ADMINISTRATION

Do not swallow. If you accidentally swallow more than used for brushing, seek professional assistance or contact a poison control center right away. If an allergic reaction develops, discontinue use immediately.

Directions

- adults and children 2 years of age and older: Brush teeth thoroughly, preferably after each meal or at least twice a day, or as directly by a dentist.
- do not swallow.
- to minimize swallowing use a pea-sized amount in children under 6.
- supervise children's brushing until good habits are established.
- children under 2 years: ask a dentist

Inactive ingredients

Glycerin, Hydrated Silica, Sodium Hexametaphosphate, Water, Flavor/Aroma, PEG-6, Zinc Stearate, Cocamidopropyl Betaine, Sodium Lauryl Sulfate, Tripotassium Phosphate, Carrageenan, Titanium Dioxide, Potassium Phosphate, Poloxamer 407, Sodium Saccharin, Algin, Tocopheryl Acetate, Xanthan Gum, Sucralose, D&C Red 33(CI 17200), FD&C Yellow 6(CI 15985), Eucalyptus Globulus Leaf Extract, Thymol

Questions?

1-866-993-4709